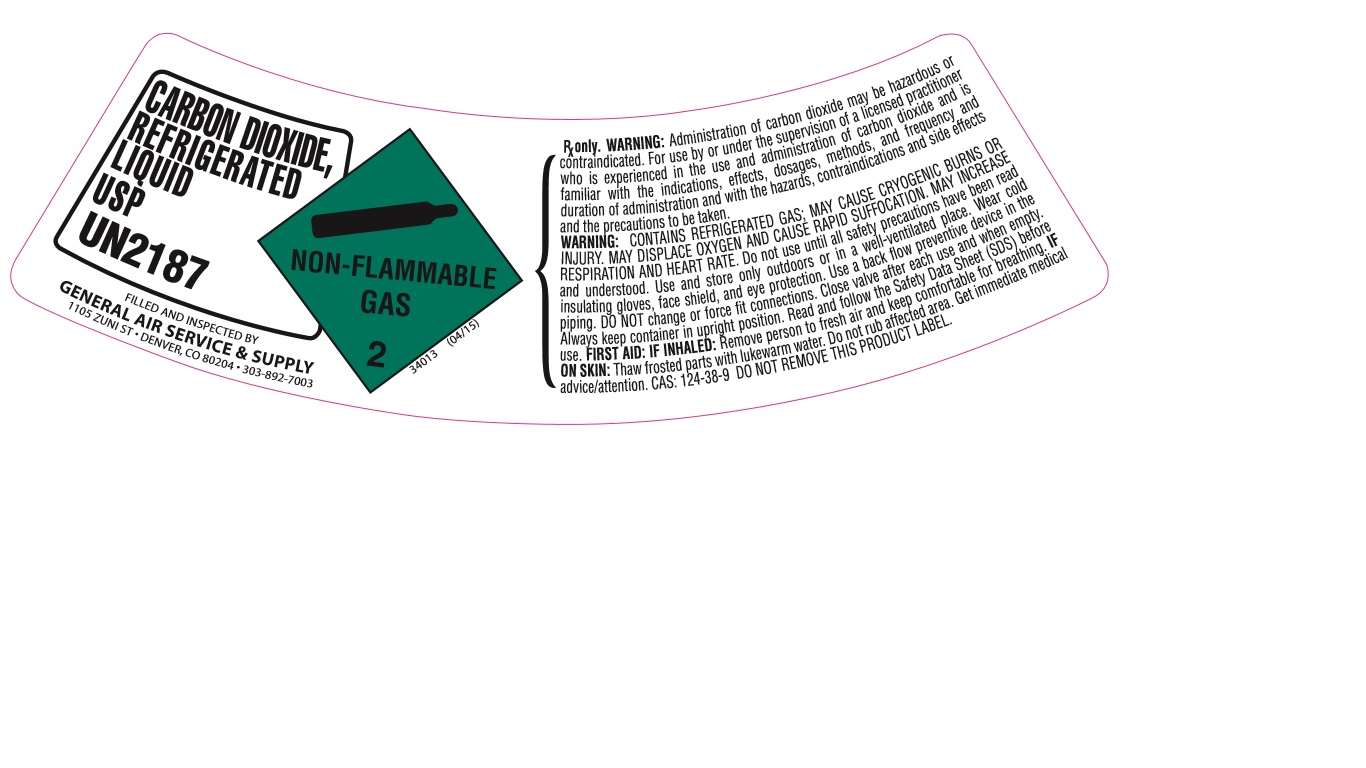 DRUG LABEL: Carbon Dioxide
NDC: 21220-123 | Form: GAS
Manufacturer: General Air Service & Supply Co.
Category: prescription | Type: HUMAN PRESCRIPTION DRUG LABEL
Date: 20251126

ACTIVE INGREDIENTS: CARBON DIOXIDE 990 mL/1 L

carbon dioxide

PACKAGE LABEL

CARBON DIOXIDE, REFRIGERATED LIQUID USP UN1013
NON-FLAMMABLE GAS 2
34013 (04/15)
FILLED AND INSPECTED BY
GENERAL AIR SERVICE & SUPPLY
1105 ZUNI ST. DENVER, CO 90204. 303-892-7003
Rx only. WARNING: Administration of Carbon dioxide may be hazardous or contraindicated. For use by or under the supervision of a licensed practitioner who is experienced in the use and administration of carbon dioxide and is familiar with the indications, effects, dosages, methods, and frequency and duration of administration, and with the hazards, contraindications, and side effects and the precautions to be taken.
WARNING: CONTAINS REFRIGERATED GAS; MAY CAUSE CRYOGENIC BURNS OR INJURY. MAY DISPLACE OXYGEN AND CAUSE RAPID SUFFOCATION. MAY INCREASE RESPIRATION AND HEART RATE. Do not use until all safety precautions have been read and understood. Use and store only outdoors or in a well-ventilated place. In case of fire: Stop leak if safe to do so. Use a back flow preventive device in the piping. Wear cold insulating gloves, face shield, and eye protection. Use a back flow preventive device in piping. DO NOT change or force fit connections. Close valve after each use and when empty. Always keep container in upright position. Read and follow the Safety Data Sheet (SDS) before use. FIRST AID: IF INHALED: Remove person to fresh air and keep comfortable for breathing. IF ON SKIN: Thaw frosted parts with lukewarm water. Do not rub affected area. Get immediate medical advice/attention. CAS: 124-38-9
DO NOT REMOVE THIS PRODUCT LABEL